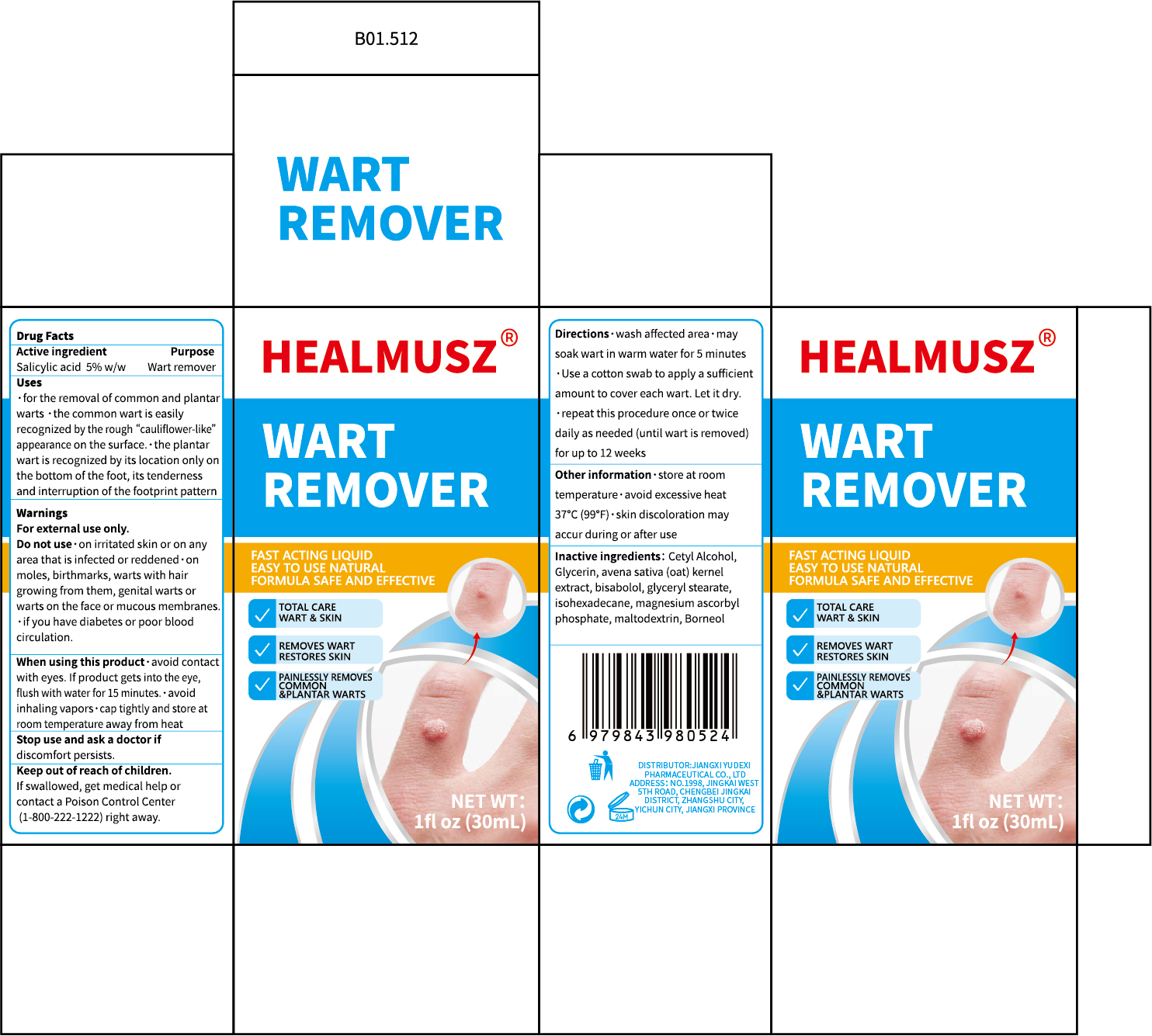 DRUG LABEL: HEALMUSZ  WART REMOVER
NDC: 85248-063 | Form: LIQUID
Manufacturer: Jiangxi Yudexi Pharmaceutical Co., LTD
Category: otc | Type: HUMAN OTC DRUG LABEL
Date: 20260206

ACTIVE INGREDIENTS: SALICYLIC ACID 5 g/100 mL
INACTIVE INGREDIENTS: ISOHEXADECANE; MALTODEXTRIN; POLYETHYLENE GLYCOL, UNSPECIFIED; AVENA SATIVA FLOWERING TOP; BISABOLOL; GLYCERIN; MAGNESIUM ASCORBYL PHOSPHATE; GLYCERYL STEARATE; BORNEOL

85248-063

Active Ingredient

Salicylic acid 5% w/w

Purpose

Wart remover

Use

·for the removal of common and plantar warts ·the common wart is easily recognized by the rough “cauliflower-like” appearance on the surface.·the plantar wart is recognized by its location only on the bottom of the foot, its tenderness and interruption of the footprint pattern

Warnings

For external use only.

Do not use

on irritated skin or on any area that is infected or reddened·on moles, birthmarks, warts with hair growing from them, genital warts or
warts on the face or mucous membranes.·if you have diabetes or poor blood circulation.

When Using

avoid contact with eyes. If product gets into the eye,flush with water for 15 minutes.·avoid inhaling vapors·cap tightly and store at
room temperature away from heat

Stop Use

Stop use and ask a doctor if discomfort persists.

Ask Doctor

Stop use and ask a doctor if discomfort persists.

Keep Oot Of Reach Of Children

If swallowed, get medical help or contact a Poison Control Center (1-800-222-1222) right away.

Directions

wash affected area·may soak wart in warm water for 5 minutes· Use a cotton swab to apply a sufficient amount to cover each wart. Let it dry.repeat this procedure once or twice daily as needed (until wart is removed)for up to 12 weeks

Other information

store at room temperature·avoid excessive heat 37°C (99°F)·skin discoloration may accur during or after use

Inactive ingredients

Cetyl Alcohol,Glycerin, avena sativa (oat) kernel extract, bisabolol, glyceryl stearate,isohexadecane, magnesium ascorbyl phosphate, maltodextrin, Borneol